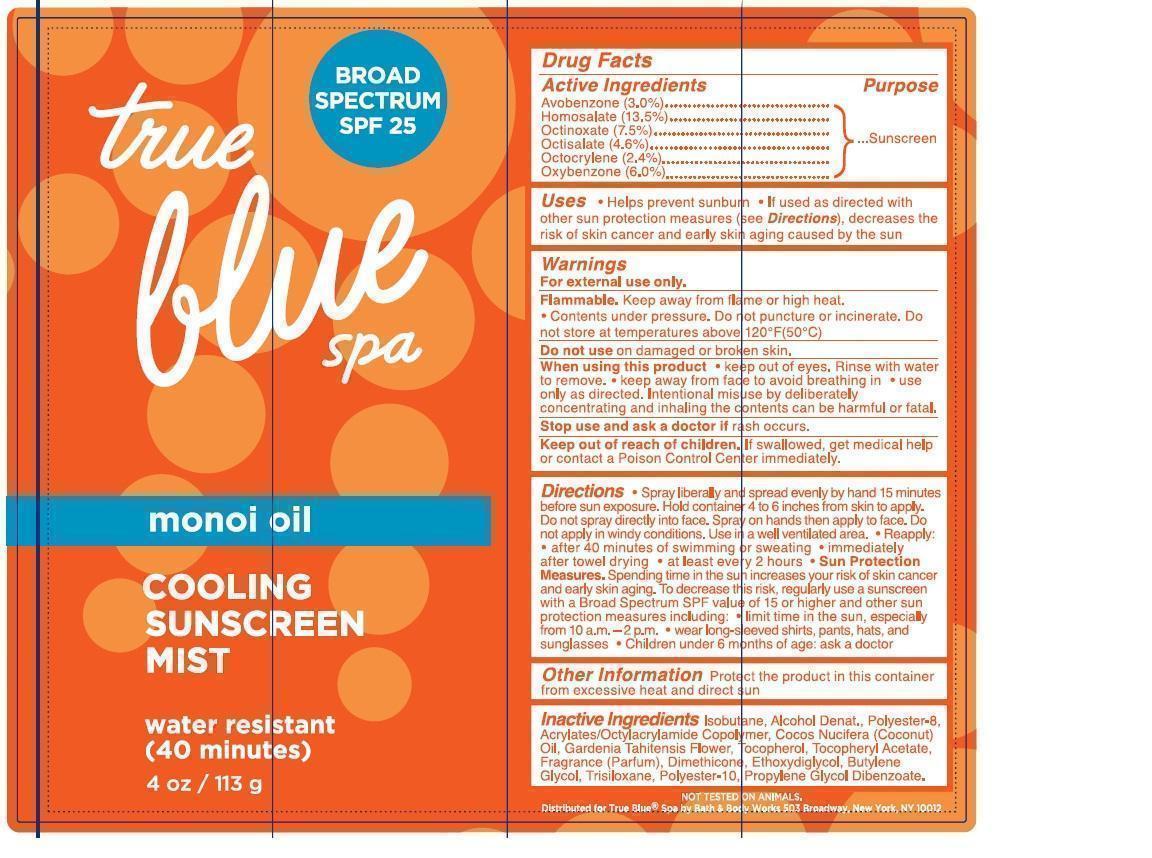 DRUG LABEL: True Blue Spa Cooling Sunscreen Mist Broad Spectrum SPF 25 Water Resistant (40 minutes) Monoi Oil
NDC: 62670-8046 | Form: AEROSOL, SPRAY
Manufacturer: Bath & Body Works, Inc.
Category: otc | Type: HUMAN OTC DRUG LABEL
Date: 20130930

ACTIVE INGREDIENTS: AVOBENZONE 3.0 mg/1 g; HOMOSALATE 13.5 mg/1 g; OCTINOXATE 7.5 mg/1 g; OCTISALATE 4.6 mg/1 g; OCTOCRYLENE 2.4 mg/1 g; OXYBENZONE 6.0 mg/1 g
INACTIVE INGREDIENTS: WATER

ACTIVE INGREDIENTS

Avobenzone 3.0%, Homosalate 13.5%, Octinoxate 7.5%, Octisalate 4.6%, Octocrylene 2.4%, Oxybenzone 6.0%

PURPOSE

Sunscreen

USES

- Helps prevent sunburn
- If used as directed with other sun protection measures (see Directions), decreases the risk of skin cancer and early skin aging caused by the sun

WARNINGS

For external use only.

FLAMMABLE

Keep away from flame or high heat.

- Contents under pressure. Do not puncture or incinerate. Do not store at temperatures above 120°F (50°C).

DO NOT USE

on damaged or broken skin.

WHEN USING THIS PRODUCT

- keep out of eyes. Rinse with water to remove.
- keep away from face to avoid breathing in
- use only as directed. Intentional misuse by deliberately concentrating and inhaling the contents can be harmful or fatal.

STOP USE AND ASK A DOCTOR IF

rash occurs.

KEEP OUT OF REACH OF CHILDREN.

If swallowed, get medical help or contact a Poison Control Center immediately.

DIRECTIONS

- Spray liberally and spread evenly by hand 15 minutes before sun exposure. Hold container 4 to 6 inches from skin to apply. Do not spray directly into face. Spray on hands then apply to face. Do not apply in windy conditions. Use in a well ventilated area.
- Reapply:
- after 40 minutes of swimming or sweating
- immediately after towel drying
- at least every 2 hours
- Sun Protection Measures. Spending time in the sun increases your risk of skin cancer and early skin aging. To decrease this risk, regularly use a sunscreen with a Broad Spectrum SPF value of 15 or higher and other sun protection measures including:
- limit time in the sun, especially from 10 a.m. - 2 p.m.
- wear long-sleeved shirts, pants, hats and sunglasses
- children under 6 months of age: ask a doctor

OTHER INFORMATION

Protect the product in this container from excessive heat and direct sun.

INACTIVE INGREDIENTS

Isobutane, Alcohol Denat., Polyester-8, Acrylates/Octylacrylamide Copolymer, Cocos Nucifera (Coconut) Oil, Gardenia Tahitensis Flower, Tocopherol, Tocopheryl Acetate, Fragrance (Parfum), Dimethicone, Ethoxydiglycol, Butylene Glycol, Trisiloxane, Polyester-10, Propylene Glycol Dibenzoate.

COMPANY INFORMATION

Bath & Body Works, Distr.

Reynoldsburg, Ohio 43068

1-800-395-1001

www.bathandbodyworks.com